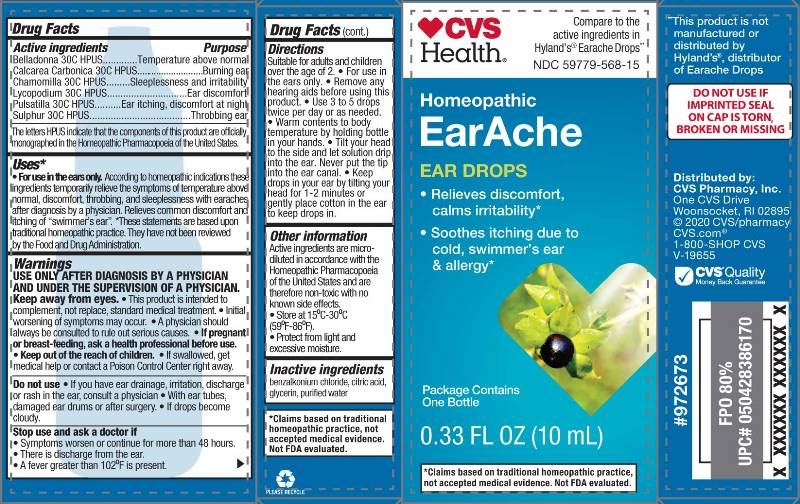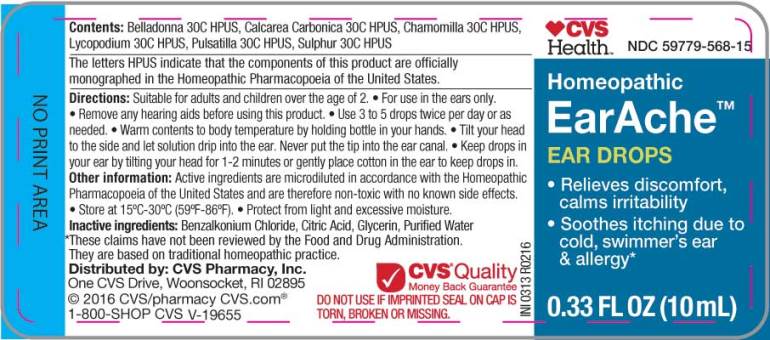 DRUG LABEL: Earache
NDC: 59779-568 | Form: LIQUID
Manufacturer: CVS Pharmacy
Category: homeopathic | Type: HUMAN OTC DRUG LABEL
Date: 20200429

ACTIVE INGREDIENTS: ATROPA BELLADONNA 30 [hp_C]/1 mL; OYSTER SHELL CALCIUM CARBONATE, CRUDE 30 [hp_C]/1 mL; MATRICARIA RECUTITA 30 [hp_C]/1 mL; LYCOPODIUM CLAVATUM SPORE 30 [hp_C]/1 mL; PULSATILLA VULGARIS 30 [hp_C]/1 mL; SULFUR 30 [hp_C]/1 mL
INACTIVE INGREDIENTS: BENZALKONIUM CHLORIDE; CITRIC ACID MONOHYDRATE; GLYCERIN; WATER

Drug Facts:

ACTIVE INGREDIENTS:

Belladonna 30C HPUS.........................Temperature above normal

Calcarea Carbonica 30C HPUS.............Burning Ear

Chamomilla 30C HPUS.......................Sleeplessness and irritability

Lycopodium Clavatum 30C HPUS.......Ear discomfort

Pulsatilla (Vulgaris) 30C HPUS............Ear itching, discomfort at night

Sulphur 30C HPUS............................Throbbing ear

The letter HPUS indicate that the components of this product are officially monographed in the Homeopathic Pharmacopoeia of the United States.

USES*:

•For use in the ears only. According to homeopathic indications these ingredients temporarily relieve the symptoms of temperature above normal, discomfort, throbbing, and sleeplessness with earaches after diagnosis by a physician. Relieves common discomfort and itching of "swimmer's ear". *These statements are based upon traditional homeopathic practice. They have not been reviewed by the Food and Drug Administration.

WARNINGS:

USE ONLY AFTER DIAGNOSIS BY A PHYSICIAN AND UNDER THE SUPERVISION OF A PHYSICIAN.

Keep away from the eyes.

• This product is intended to complement, not replace standard medical treatment. • Initial worsening of the symptoms may occur.

• A physician should always be consulted to rule out serious causes.

• If pregnant or breast-feeding, ask a health professional before use.

• Keep out of the reach of children.

• If swallowed, get medical help or contact a Poison Control Center right away.

Do not use

• If you have ear drainage, irritation, discharge or rash in the ear, consult a physician.

• With ear tubes, damaged ear drums or after surgery.

• If drops become cloudy.

Stop use and ask a doctor if

• Symptoms worsen or continue for more than 48 hours.

• There is discharge from the ear.

• A fever greater than 102°F is present.

OTHER SAFETY INFORMATION:

Active ingredients are micro-diluted in accordance with the Homeopathic Pharmacopoeia of the United States and are therefore non-toxic with no known side effects.

• Store at 15°C-30°C (59°F-86°F).

• Protect from light and excessive moisture.

†Claims based on traditional homeopathic practice, not accepted medical evidence. Not FDA evaluated.

DO NOT USE IF INPRINTED SEAL ON CAP IS TORN, BROKEN OR MISSING.

KEEP OUT OF REACH OF CHILDREN:

Keep out of the reach of children. If swallowed, get medical help or contact a Poison Control Center right away.

DIRECTIONS:

Suitable for adults and children over the age of 2.

• For use in the ears only.

• Remove any hearing aids before using this product.

• Use 3 to 5 drops twice per day or as needed.

• Warm contents to body temperature by holding bottle in your hands.

• Tilt your head to the side and let solution drip into the ear. Never put the tip into the ear canal.

• Keep drops in your ear by tilting your head for 1-2 minutes or gently place cotton in the ear to keep drops in.

INDICATIONS:

•For use in the ears only. According to homeopathic indications these ingredients temporarily relieve the symptoms of temperature above normal, discomfort, throbbing, and sleeplessness with earaches after diagnosis by a physician. Relieves common discomfort and itching of "swimmer's ear". *These statements are based upon traditional homeopathic practice. They have not been reviewed by the Food and Drug Administration.

INACTIVE INGREDIENTS:

benzalkonium chloride, citric acid, glycerin, purified water

QUESTIONS:

Distributed by: CVS Pharmacy, Inc.

One CVS Drive

Woonsocket, RI 02895

©2020 CVS/Pharmacy

CVS.com

1-800-SHOP CVS

V-19655

PACKAGE LABEL DISPLAY:

CVS

Health

Compare to the

active ingredients in

Hyland's® Earache Drops

NDC 59779-568-15

Homeopathic

EarAche

EAR DROPS

• Relieves discomfort,

calms irritability*

• Soothes itching due to

cold, swimmer's ear

& allergy*

Package Contains

One Bottle

0.33 FL OZ (10mL)